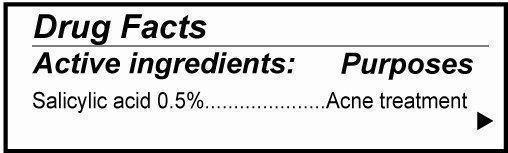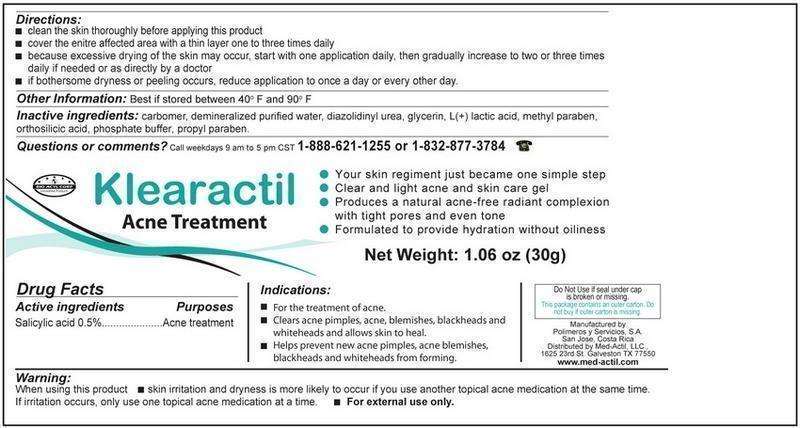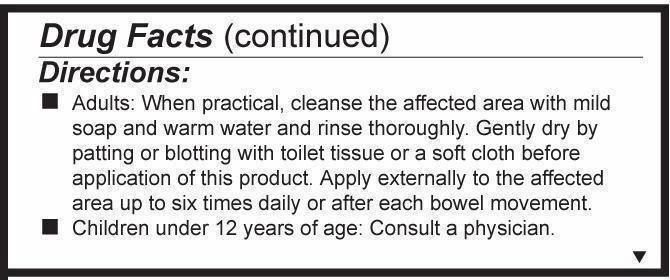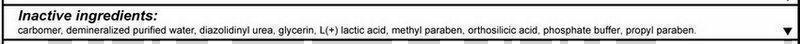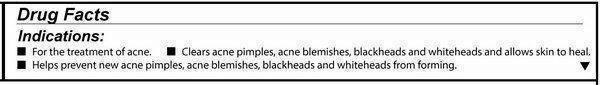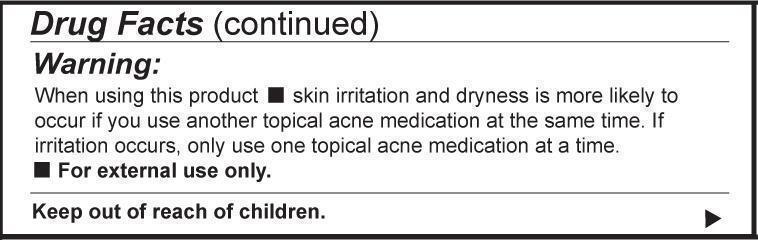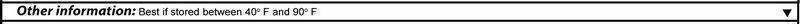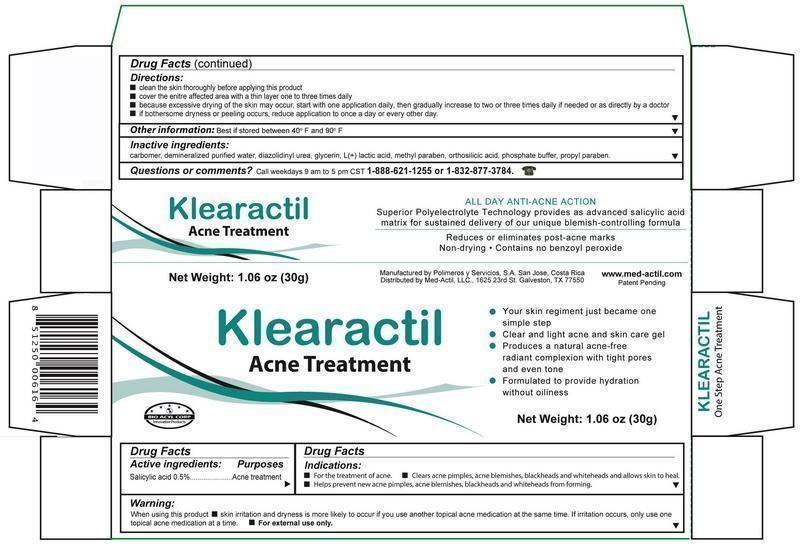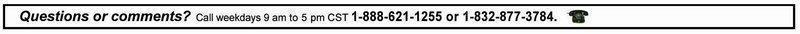 DRUG LABEL: KLEARACTIL
NDC: 69492-012 | Form: GEL
Manufacturer: POLIMEROS Y SERVICIOS S.A.
Category: otc | Type: HUMAN OTC DRUG LABEL
Date: 20190315

ACTIVE INGREDIENTS: SALICYLIC ACID 5 mg/1 g
INACTIVE INGREDIENTS: CARBOXYPOLYMETHYLENE; DIAZOLIDINYL UREA; GLYCERIN; LACTIC ACID, L-; METHYLPARABEN; ORTHOSILICIC ACID; SODIUM PHOSPHATE, DIBASIC; PROPYLPARABEN; WATER

Submission for Klearactil Acne Topical Treatment

Detail showing Active Ingredient from package

Active ibgredients_001.jpg

Information shown both on container label and paclage

Detail showing Inactive ingredient from package

Inactive ingredients.jpg

Information shown both on container label and paclage

Detail showing Purpose within Active Ingredients from package

Purpose.jpg

Information shown both on container label and package

Detail showing Instructions for use and named Directions from package

indications_001.jpg

Information shown both on container label and package

Detail showing Dosage and Administration within Directions from package

Dosage and administration.jpg

Information shown both on container lable and package

Detail showing Warnings from package

Warnings.jpg

nformation shown both on container label and package

Detail showing Keep Out of Reach of Children within Warnings from package

Keep out of reach of Childreb.jpg

Information shown on package

Detail showing Questions from package

Questions.jpg

Information shown both on container label and package

etail showing Other Safety Information from package

Other safety information.jpg

nformation shown both on container label and package

Representative sample image of carton/container label

Container label.jpg

General view of inner container label

Package label.jpg

General view of box content of labeling